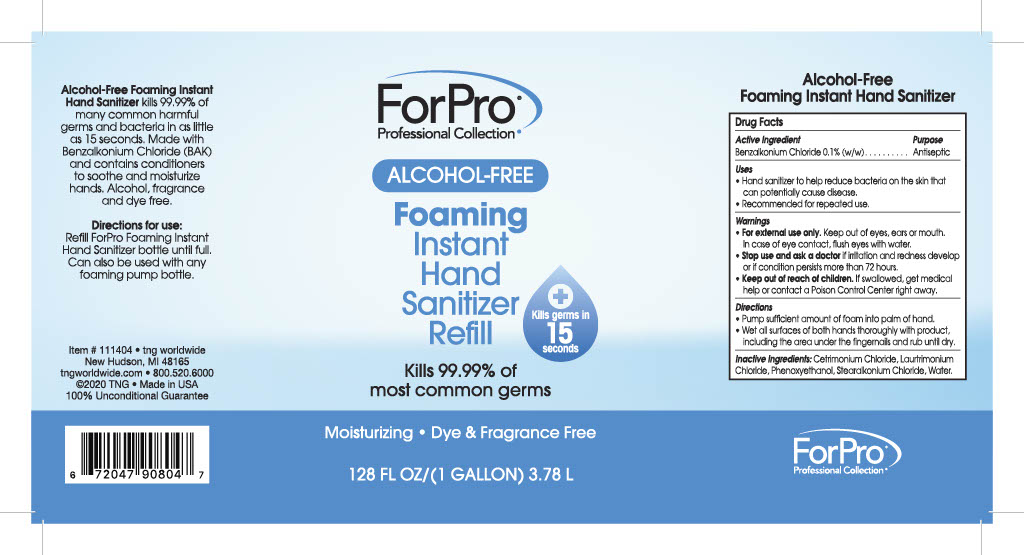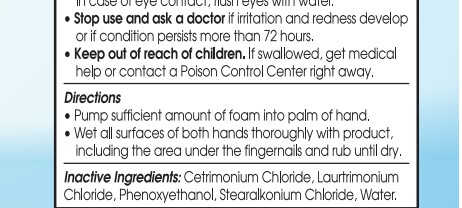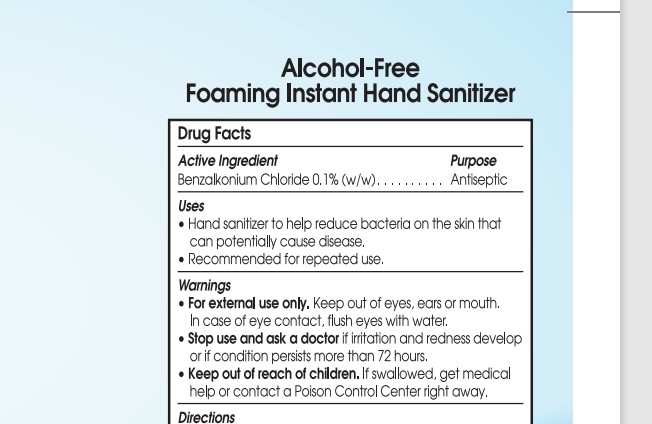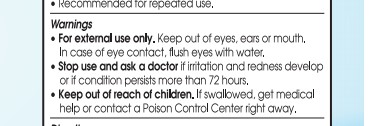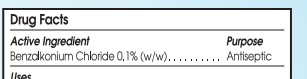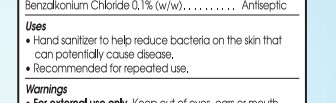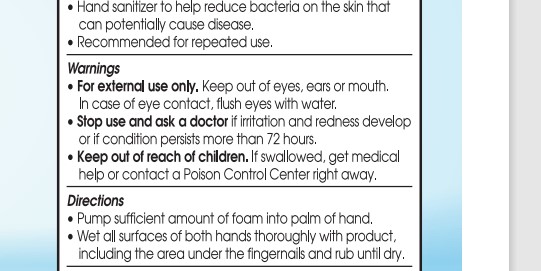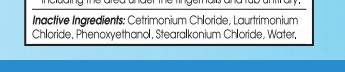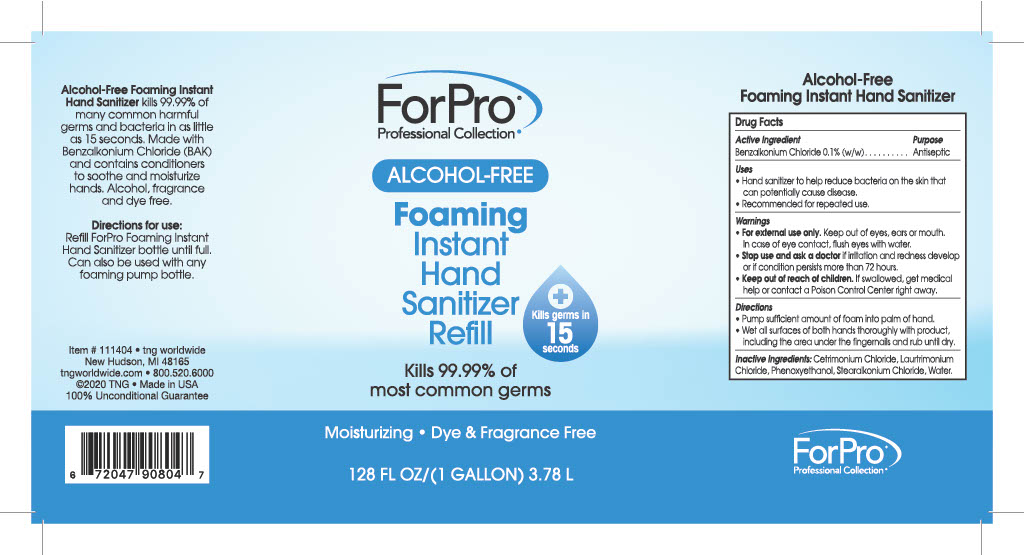 DRUG LABEL: ForPro Professional Collection Alcohol-Free Foaming Instant Hand Sanitizer
NDC: 72671-100 | Form: LIQUID
Manufacturer: Sani-care Salon Products, Inc.
Category: otc | Type: HUMAN OTC DRUG LABEL
Date: 20240709

ACTIVE INGREDIENTS: BENZALKONIUM CHLORIDE 0.1 g/100 mL
INACTIVE INGREDIENTS: WATER 99.9 mL/100 mL

ForPro Foaming Instant Hand Sanitizer